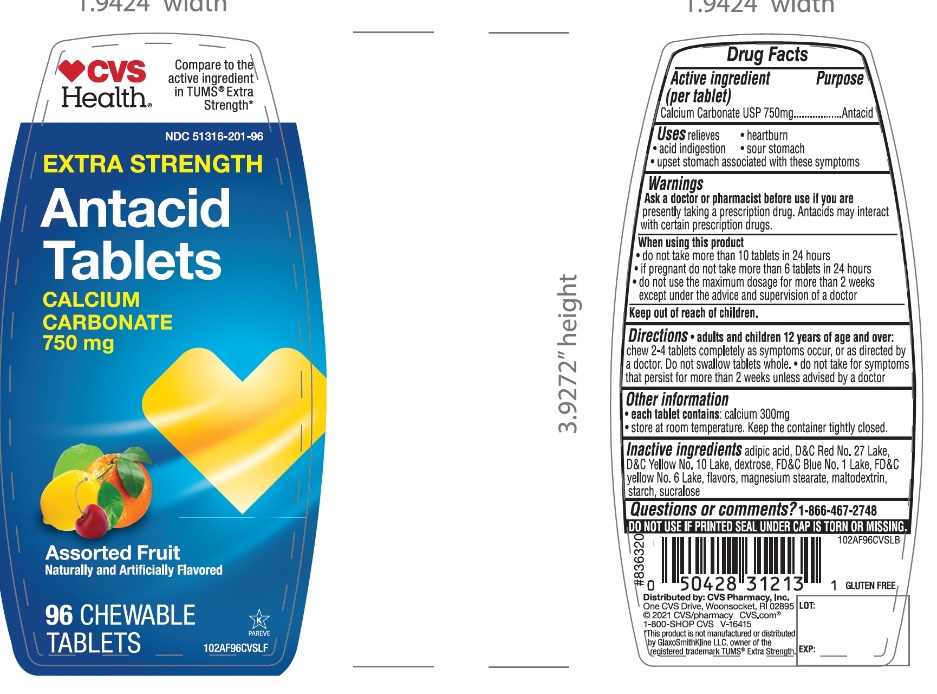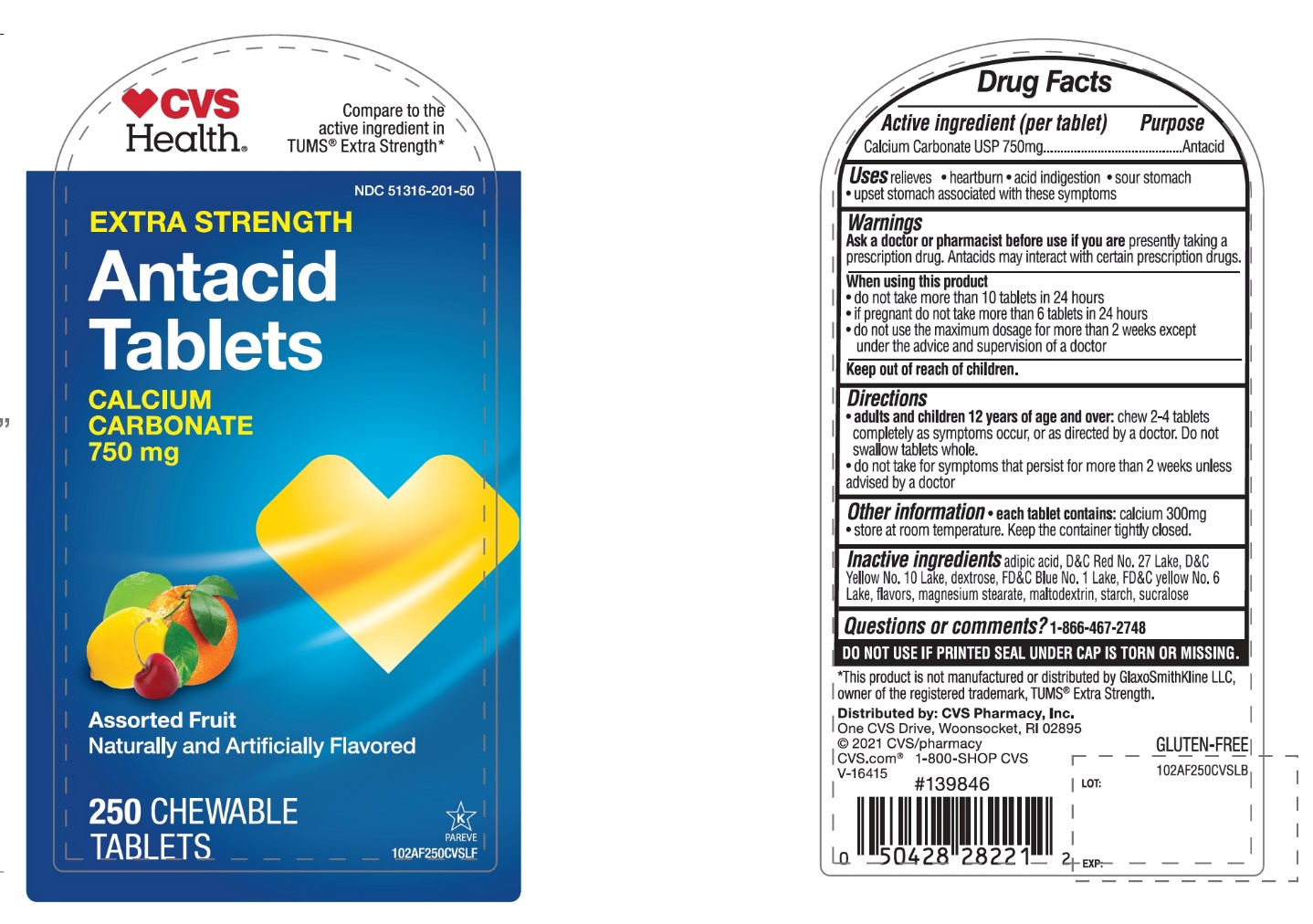 DRUG LABEL: CVS PHARMACY,INC.

NDC: 51316-201 | Form: TABLET, CHEWABLE
Manufacturer: CVS PHARMACY,INC.
Category: otc | Type: HUMAN OTC DRUG LABEL
Date: 20251204

ACTIVE INGREDIENTS: CALCIUM CARBONATE 750 mg/1 1
INACTIVE INGREDIENTS: ADIPIC ACID; FD&C BLUE NO. 1; DEXTROSE, UNSPECIFIED FORM; MAGNESIUM STEARATE; MALTODEXTRIN; D&C RED NO. 27; STARCH, CORN; SUCRALOSE; FD&C YELLOW NO. 6; D&C YELLOW NO. 10

CVS Extra Strength Antacid Tablets Drug Facts

Active ingredient

Calcium Carbonate USP 750mg

Purpose

Antacid

Uses

relieves:

• heartburn

• sour stomach

• acid indigestion

• upset stomach associated with these symptoms

Warnings

Ask a doctor or pharmacist before use if you aretaking a prescription drug. Antacids may interact with certain prescription drugs.

When using this product

• do not take more than 10 tablets in 24 hours

• if pregnant do not take more than 6 tablets in 24 hours

• do not use the maximum dosage for more than 2 weeks except under the advice and supervision of a doctor.

Directions

• adults and children 12 years of age and over:chew 2-4 tablets completely as symptoms occur, or as directed by a doctor. Do not swallow tablets whole.

• do not take for symptoms that persist for more than 2 weeks unless advised by a doctor

Other Information

• e ach tablets contains:calcium 300mg

• Store at room temperature. Keep the container tightly closed

Inactive ingredients

adipic acid, D&C Red No. 27 Lake, D&C Yellow No. 10 Lake, dextrose, FD&C Blue No. 1 Lake, FD&C Yellow no. 6 Lake, flavors, magnesium stearate, maltodextrin, starch, sucralose.

Questions or comments?

1-866-467-2748

SAFETY SEALED: DO NOT USE IF PRINTED SEAL UNDER CAP IS TORN OR MISSING

Package/Label Principal Display Panel

*Compare to the active ingredient in Extra Strength Tums®

NDC 51316-201-96

EXTRA STRENGTH

Antacid Tablets

Calcium Carbonate 750 mg

Fast Relief of Upset Stomach, Heartburn, and Acid Indigestion

Assorted Fruit

Naturally and Artificially Flavored

96 Chewable Tablets

Distributed by

*This product is not manufactured or distributed by GlaxoSmithKline LLC, owner of the registered trademark, Extra Strength Tums®

Package Label for 96 Chewable tablets